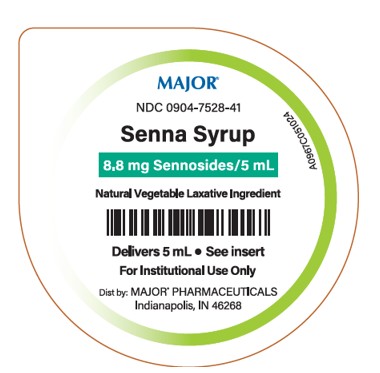 DRUG LABEL: Senna
NDC: 0904-7528 | Form: LIQUID
Manufacturer: Major Pharmaceuticals
Category: otc | Type: HUMAN OTC DRUG LABEL
Date: 20250718

ACTIVE INGREDIENTS: SENNOSIDES 8.8 mg/5 mL
INACTIVE INGREDIENTS: CITRIC ACID; GLYCERIN; METHYLPARABEN; POTASSIUM SORBATE; PROPYLPARABEN; WATER; SUCROSE

Senna

Active ingredient (per teaspoonful - 5 mL) Purpose

Sennosides 8.8 mg Laxative

Uses

- relieves occasional constipation (irregularity)
- generally causes bowel movement in 6 to 12 hours

Warnings

Do not use

• laxative products for longer than 1 week unless directed by a doctor.

Ask a doctor or pharmacist before use if you have

• stomach pain • nausea • vomiting
• noticed a change in bowel movement that continues over a period of 2 weeks

Stop use and ask a doctor if

you have rectal bleeding or failure to have a bowel movement after use of laxative. These may indicate a serious condition.

If pregnant or breastfeeding,

ask a health professional before use.

Keep out of reach of children

In case of accidental overdose, get medical help or contact a Poison Control Center (1-800-222-1222) immediately.

Directions

• shake well before using • Do not exceed recommended dose

Age | Starting Dose | Maximum Dose
adults and children 12 years and older | 2 to 3 teaspoonfuls once a day preferably at bedtime; increase as needed or as recommended by a doctor | 3 teaspoons in the morning and 3 teaspoons at bedtime
Under 12 years of age | ask a doctor | ask a doctor

Other Information

- store at room temperature 20° to 25°C (68° to 77°F).
- a brown, natural flavored syrup supplied in the following oral dosage form:

NDC 0904-7528-41: 5 mL unit dose cup, in a tray of ten cups.
NDC 0904-7528-94: Case contains 40 unit dose cups of 5 mL (0904-7528-41) packaged in 4 trays of 10 unit dose cups each.

Inactive ingredients:

citric acid, glycerin, methylparaben, potassium sorbate, propylparaben, purified water, and sucrose.

Questions or comments?

Call 1-800-845-8210.

Distributed by:

R10/24

MAJOR® PHARMACEUTICALS
Indianapolis, IN 46268

Principal Display Panel

Major®
NDC 09045-7528-41
Senna Syrup
8.8 mg Sennosides/5 mL